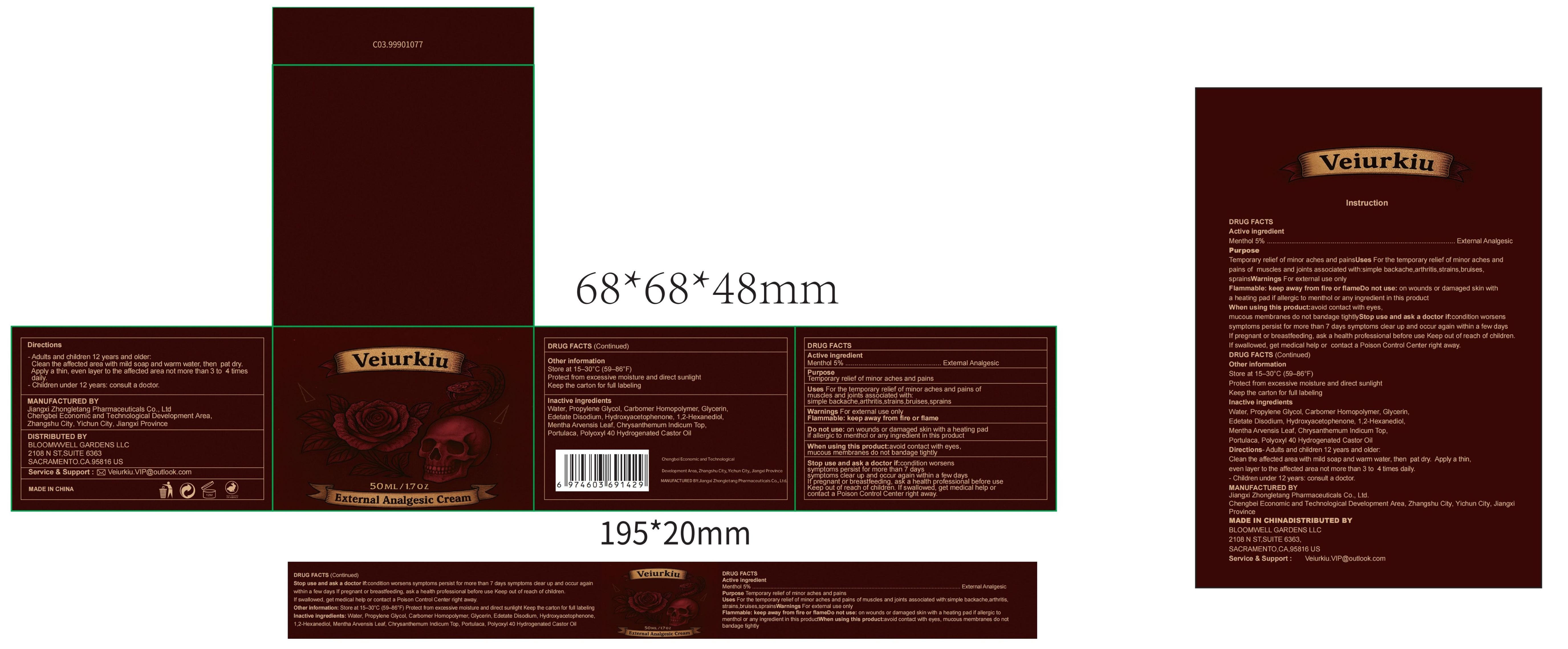 DRUG LABEL: External Analgesic Cream with Menthol 5%
NDC: 85284-010 | Form: CREAM
Manufacturer: BLOOMWELL GARDENS LLC
Category: otc | Type: HUMAN OTC DRUG LABEL
Date: 20260218

ACTIVE INGREDIENTS: MENTHOL 5 g/100 g
INACTIVE INGREDIENTS: HYDROXYACETOPHENONE; WATER; POLYOXYL 40 HYDROGENATED CASTOR OIL; PORTULACA GRANDIFLORA LEAF; PROPYLENE GLYCOL; CARBOMER HOMOPOLYMER, UNSPECIFIED TYPE; GLYCERIN; EDETATE DISODIUM; CHRYSANTHEMUM INDICUM TOP; MENTHA ARVENSIS LEAF; 1,2-HEXANEDIOL

Active ingredient

Menthol 5%

INACTIVE INGREDIENT

Water, Propylene Glycol, Carbomer Homopolymer, Glycerin,

Edetate Disodium, Hydroxyacetophenone, 1,2-Hexanediol,

Mentha Arvensis Leaf, Chrysanthemum Indicum Top,

Portulaca, Polyoxyl 40 Hydrogenated Castor Oil

INDICATIONS AND USAGE

For the temporary relief of minor aches and pains of muscles and joints associated with: simple backache, arthritis, strains, bruises, sprains

WARNINGS

For external use only

WHEN USING

avoid contact with eyes,

mucous membranes do not bandage tightly

Stop use and ask a doctor if: condition worsens

symptoms persist for more than 7 days

symptoms clear up and occur again within a few days

Keep out of reach of children. If swallowed, get medical help or

contact a Poison Control Center right away

PREGNANCY OR BREAST FEEDING

If pregnant or breastfeeding, ask a health professional before use

DOSAGE AND ADMINISTRATION

- Adults and children 12 years and older:

Clean the affected area with mild soap and warm water, then pat dry.

Apply a thin, even layer to the affected area not more than 3 to 4 times

daily.

- Children under 12 years: consult a doctor

PURPOSE

Temporary relief of minor aches and pains

DO NOT USE

on wounds or damaged skin with a heating pad

if allergic to menthol or any ingredient in this product

OTHER SAFETY INFORMATION

Store at 15–30°C (59–86°F)

Protect from excessive moisture and direct sunlight

Keep the carton for full labeling

Flammable: keep away from fire or flame